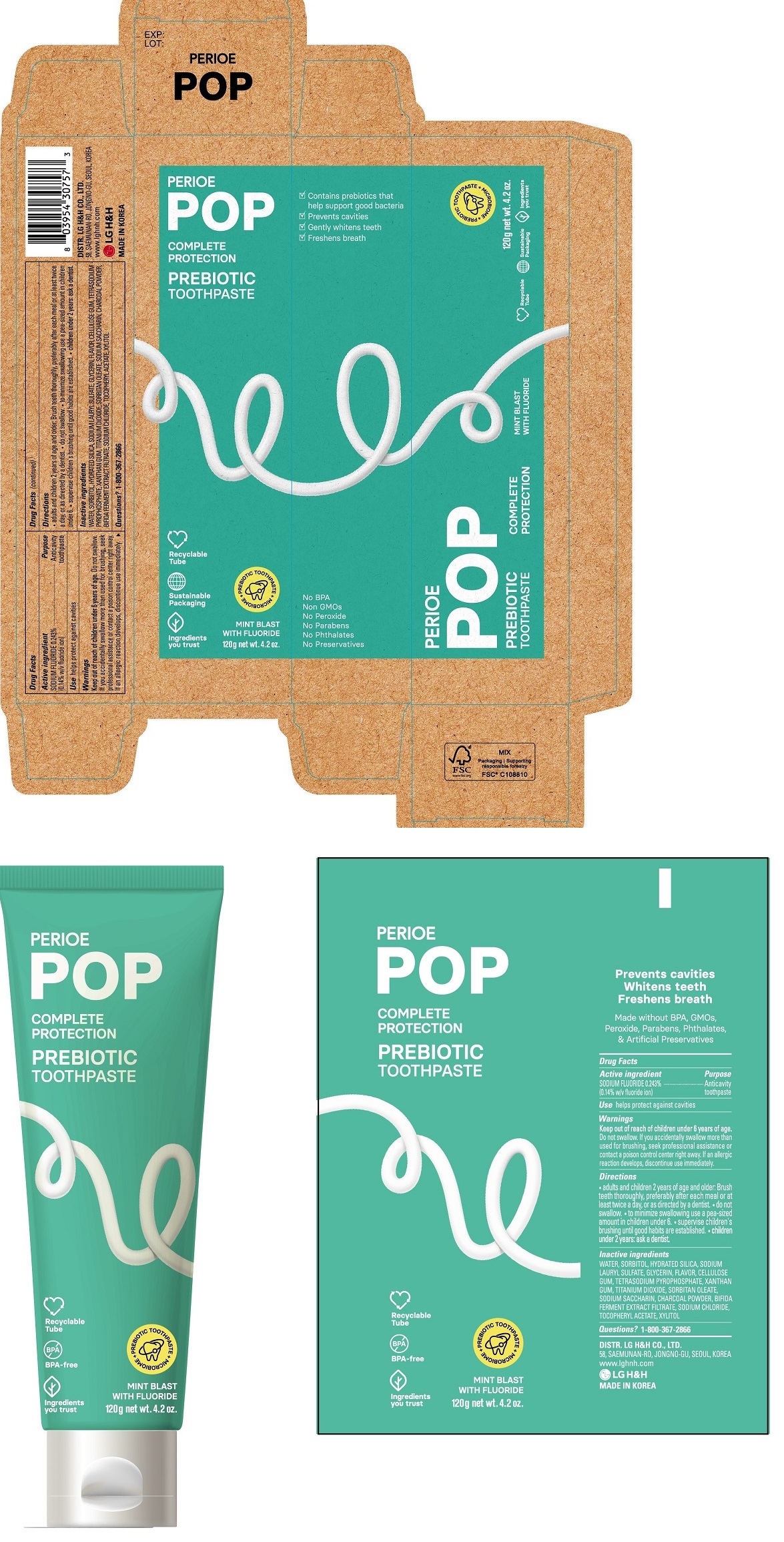 DRUG LABEL: PERIOE POP Complete Protection Prebiotic
NDC: 43136-603 | Form: PASTE, DENTIFRICE
Manufacturer: Tai Guk Pharm. Co., Ltd.
Category: otc | Type: HUMAN OTC DRUG LABEL
Date: 20250101

ACTIVE INGREDIENTS: SODIUM FLUORIDE 1.4 mg/1 g
INACTIVE INGREDIENTS: MICA; HYDRATED SILICA; GLYCERIN; WATER; CARBOXYMETHYLCELLULOSE SODIUM; SODIUM LAURYL SULFATE; XYLITOL; SACCHARIN SODIUM; SORBITAN MONOOLEATE; TITANIUM DIOXIDE; SODIUM CHLORIDE; XANTHAN GUM; ACTIVATED CHARCOAL; SODIUM PYROPHOSPHATE; .ALPHA.-TOCOPHEROL ACETATE, DL-; SORBITOL

PERIOE POP Complete Protection Prebiotic Toothpaste Mint Blast 120 g

Drug Facts

Active Ingredient

SODIUM FLUORIDE 0.243% (0.14% w/v fluoride ion)

Purpose

Anticavity toothpaste

Use

- helps protect against cavities

Warnings

Keep out of reach of children under 6 years of age.
Do not swallow. If you accidentally swallow more than used for brushing, seek professional assistance or contact a Poison Control Center right away. If an allergic reaction develops, discontinue use immediately.

Directions

- adults and children 2 years of age and older: Brush teeth thoroughly, preferably after each meal or at least twice a day, or as directed by a dentist.
- do not swallow
- to minimize swallowing use a pea-sized amount in children under 6
- supervise children's brushing until good habits are established.
- children under 2 years: ask a dentist.

Inactive Ingredients

WATER, SORBITOL, HYDRATED SILICA, SODIUM LAURYL SULFATE, GLYCERIN, FLAVOR, CELLULOSE GUM, TETRASODIUM PYROPHOSPHATE, XANTHAN GUM, TITANIUM DIOXIDE, SORBITAN OLEATE, SODIUM SACCHARIN, CHARCOAL POWDER, BIFIDA FERMENT EXTRACT FILTRATE, SODIUM CHLORIDE, TOCOPHERYL ACETATE, XYLITOL

Questions?

1-800-367-2866

Distributed by

DISTR. LG H&H CO., LTD.
58, SAEMUNAN-RO, JONGNO-GU, SEOUL, KOREA
www.lghnh.com
LG H&H
MADE IN KOREA

Principal Display Panel - 120 g Tube Carton

PERIOE

POP

COMPLETE
PROTECTION

PREBIOTIC
TOOTHPASTE

MINT BLAST
WITH FLUORIDE

120g net wt. 4.2 oz.